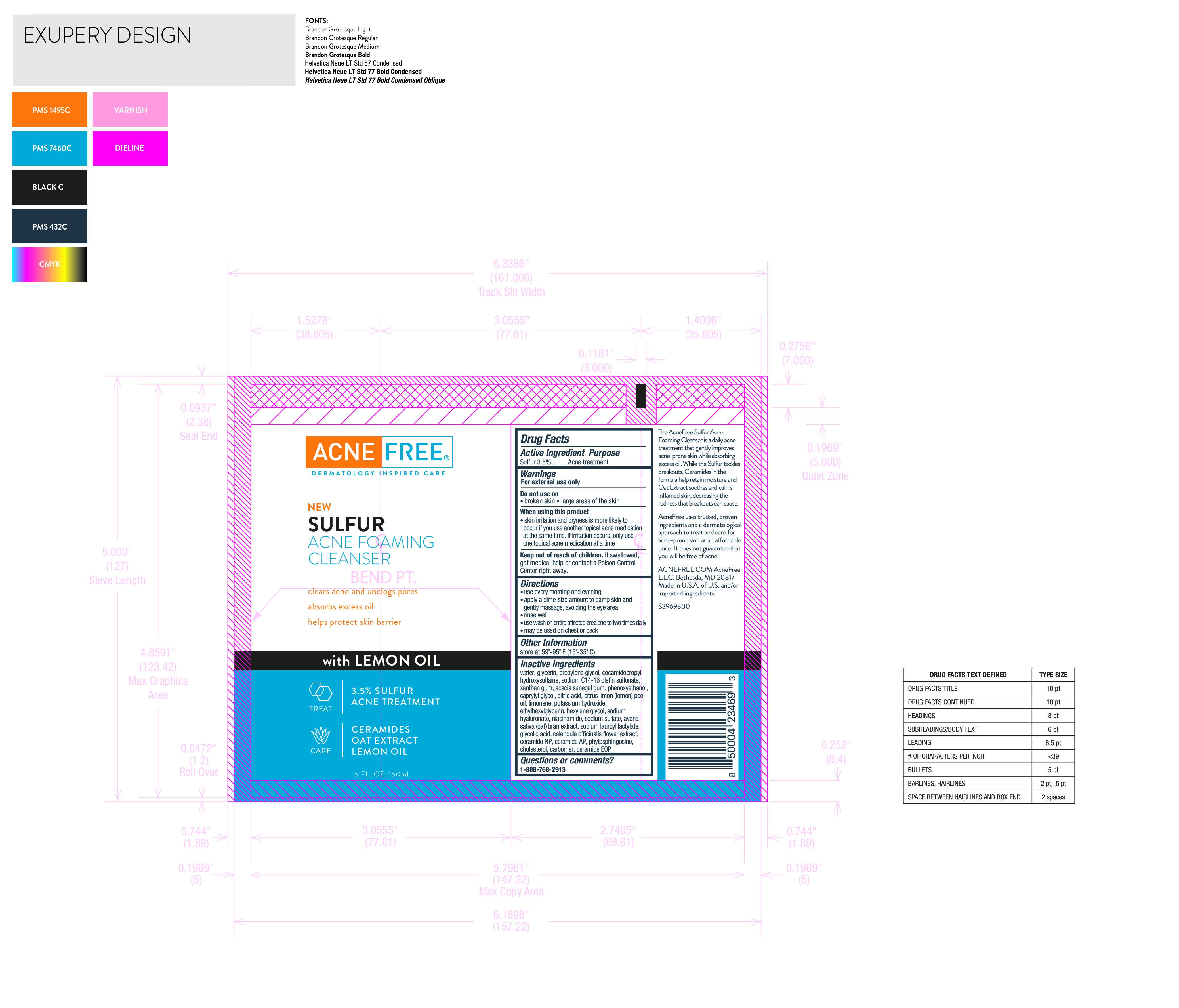 DRUG LABEL: Sulfur Acne Foaming Cleanser
NDC: 80861-113 | Form: CREAM
Manufacturer: Acne Free, LLC
Category: otc | Type: HUMAN OTC DRUG LABEL
Date: 20250724

ACTIVE INGREDIENTS: SULFUR 0.001 g/1 g
INACTIVE INGREDIENTS: GLYCERIN; PROPYLENE GLYCOL

Sulfur Acne Foaming Cleanser

Active Ingredient

Sulfur 3.5 percent

Purpose

Acne Treatment

Warnings

For external use only

Do not use on

broken skin

large areas of skin

INDICATIONS AND USAGE

FOR EXTERNAL USE ONLY

When using this product

skin irritation and dryness is more likely to occur if you use another topical acne medication at the same time.

If irritation occurs, only use one topical acne medication at a time

Keep out of reach of children

If swallowed, get medical help or contact a Poison Control Center right away

Directions

use every morning and evening

• apply a dime-size amount to damp skin and gently massage, avoiding the eye area

• rinse well

• use wash on entire affected area one to two times daily

• may be used on chest or back

Other Information

store at 59˚-95˚ F (15˚-35˚ C

Inactive Ingredients

water, glycerin, propylene glycol, cocamidopropyl hydroxysultaine, sodium C14-16 olefin sulfonate, xanthan gum, acacia senegal gum, phenoxyethanol, caprylyl glycol, citric acid, citrus limon (lemon) peel oil, limonene, potassium hydroxide, ethylhexylglycerin, hexylene glycol, sodium hyaluronate, niacinamide, sodium sulfate, avena sativa (oat) bran extract, sodium lauroyl lactylate, glycolic acid, calendula officinalis flower extract, ceramide NP, ceramide AP, phytosphingosine, cholesterol, carbomer, ceramide EOP

Questions or comments?

1-888-768-2913